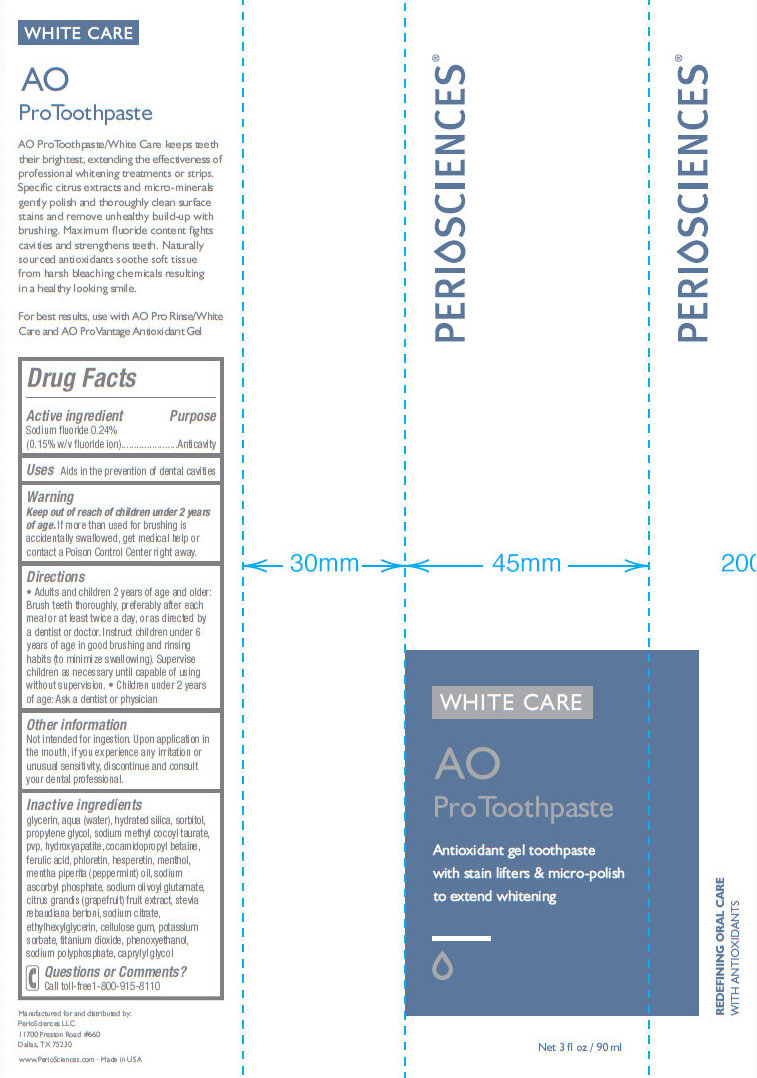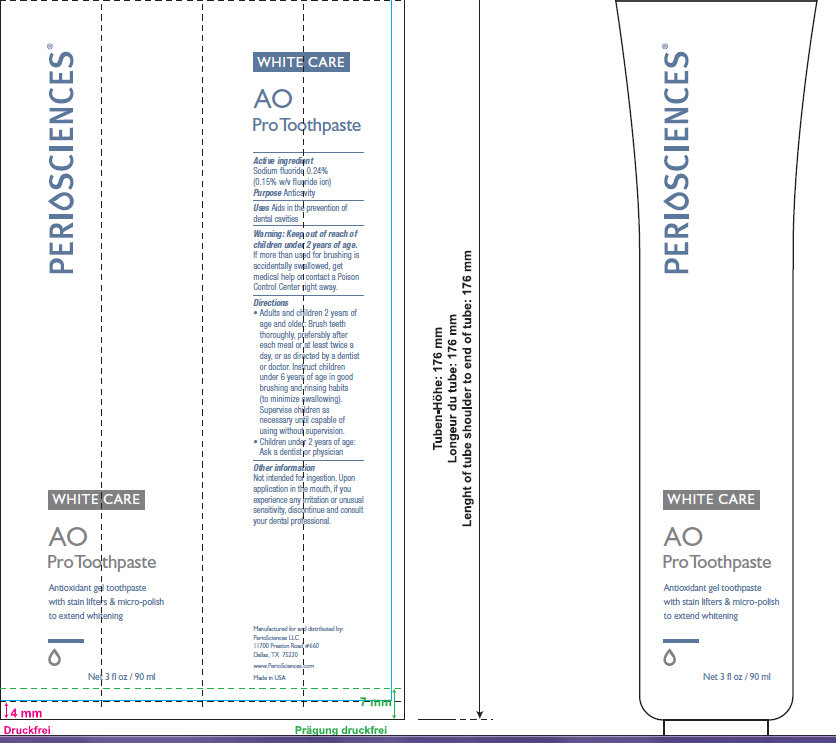 DRUG LABEL: PERIOSCIENCES White Care AO Pro
NDC: 53238-001 | Form: PASTE, DENTIFRICE
Manufacturer: PERIOSCIENCES LLC
Category: otc | Type: HUMAN OTC DRUG LABEL
Date: 20260209

ACTIVE INGREDIENTS: SODIUM FLUORIDE 0.24 mg/100 mL
INACTIVE INGREDIENTS: WATER; HYDRATED SILICA; SORBITOL; PROPYLENE GLYCOL; SODIUM METHYL COCOYL TAURATE; TRIBASIC CALCIUM PHOSPHATE; COCAMIDOPROPYL BETAINE; FERULIC ACID; PHLORETIN; HESPERETIN; MENTHOL; PEPPERMINT OIL; SODIUM ASCORBYL PHOSPHATE; PUMMELO; STEVIA REBAUDIANA WHOLE; SODIUM CITRATE; ETHYLHEXYLGLYCERIN; CARBOXYMETHYLCELLULOSE SODIUM; POTASSIUM SORBATE; TITANIUM DIOXIDE; PHENOXYETHANOL; SODIUM POLYMETAPHOSPHATE; CAPRYLYL GLYCOL

PERIOSCIENCES White Care AO Pro Toothpaste

Active ingredient

Sodium fluoride 0.24%
(0.15% w/v fluoride ion)

Purpose

Anticavity

Uses

Aids in prevention of dental cavities.

Warning

Keep out of reach of children under 2 years of age.

If more than used for brushing is accidentally swallowed, get medical help or contact a Poison Control Center right away.

Directions

- Adults and children 2 years of age and older: Brush teeth thoroughly, preferably after each meal or at least twice a day, or as directed by a dentist or doctor. Instruct children under 6 years of age in good brushing and rinsing habits (to minimize swallowing). Supervise children as necessary until capable of using without supervision.
- Children under 2 years of age: Ask a dentist or physician

Other information

Not intended for ingestion. Upon application in the mouth, if you experience any irritation or unusual sensitivity, discontinue and consult your dental professional.

Inactive ingredients

glycerin, aqua (water), hydrated silica, sorbitol, propylene glycol, sodium methyl cocoyl taurate, pvp, hydroxyapatite, cocamidopropyl betaine, ferulic acid, phloretin, hesperetin, menthol, mentha piperita (peppermint) oil, sodium ascorbyl phosphate, sodium olivoyl glutamate, citrus grandis (grapefruit) fruit extract, stevia rebaudiana bertoni, sodium citrate, ethylhexylglycerin, cellulose gum, potassium sorbate, titanium dioxide, phenoxyethanol, sodium polyphosphate, caprylyl glycol

Questions or Comments?

Call toll-free 1-800-915-8110

PACKAGE LABEL

PERIOSCIENCES WHITE CARE AO Pro Toothpaste Antioxidant gel toothpaste with stain lifters and micro-polish to extend whitening Net 3 fl oz / 90 ml Manufactured for and distributed by: PerioSciences LLC 11700 Preston Road #660 Dallas, TX 75230 www.PerioSciences.com Made in USA